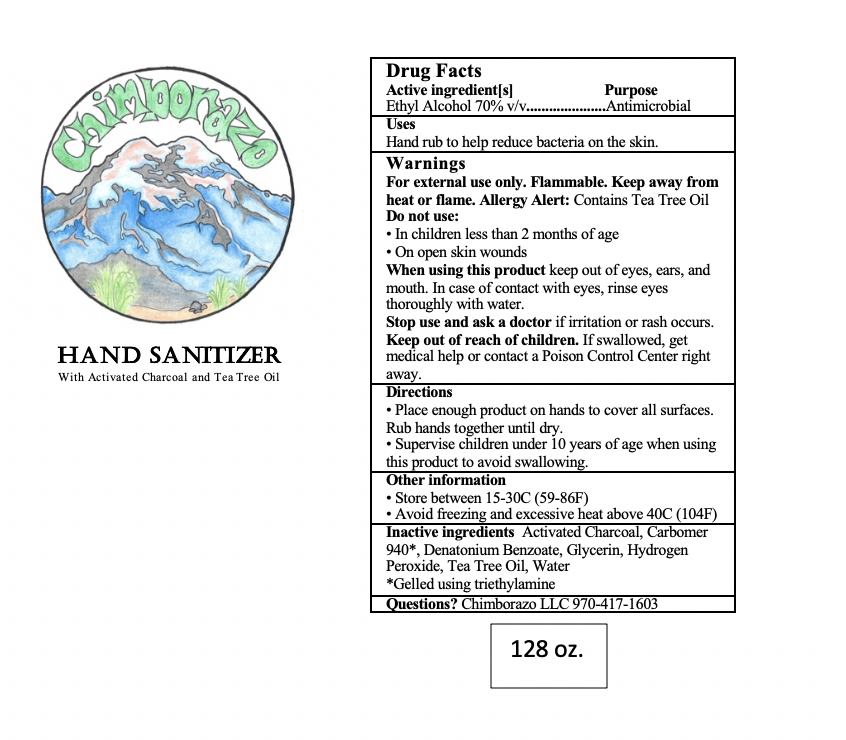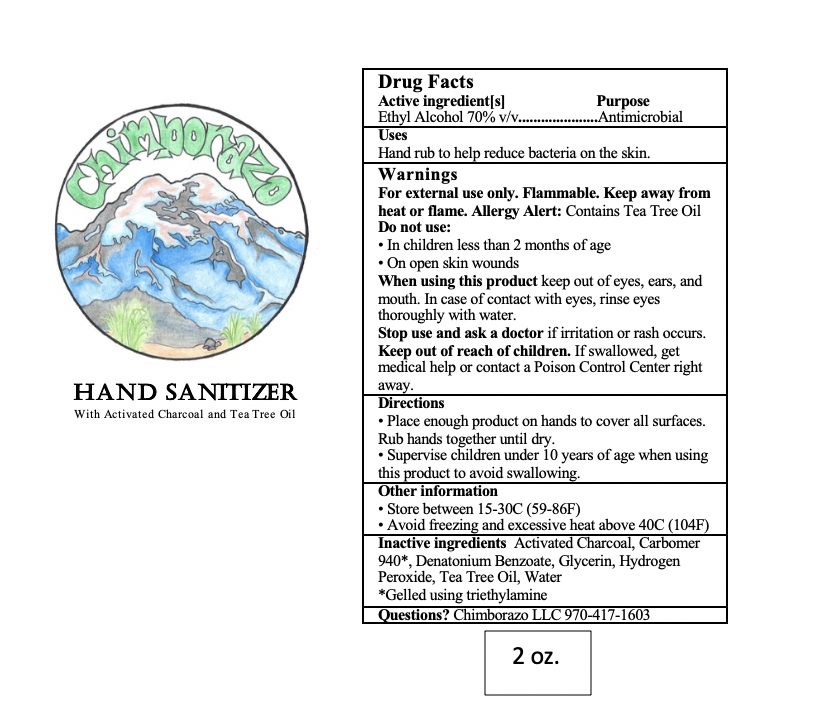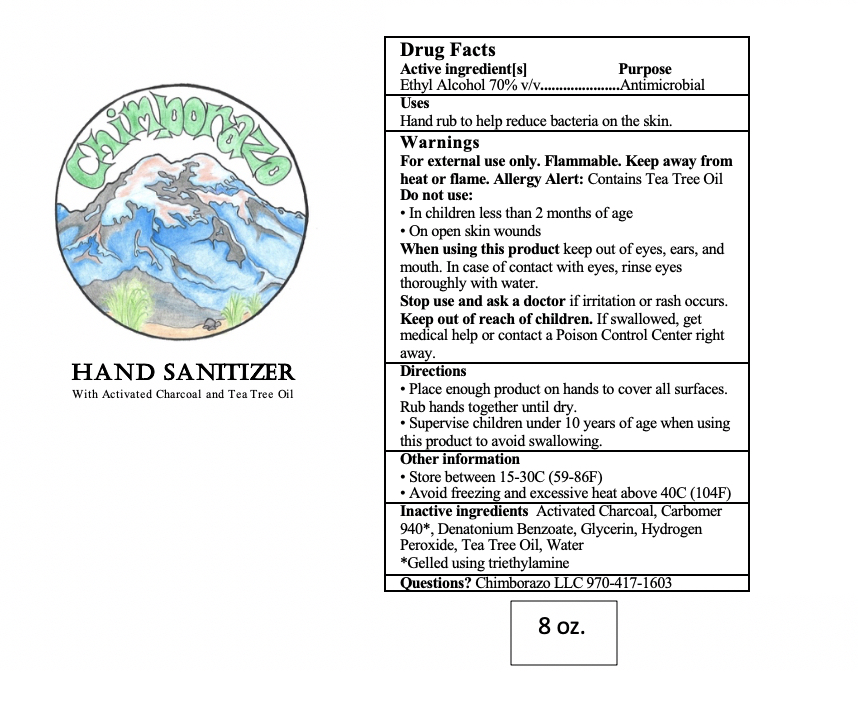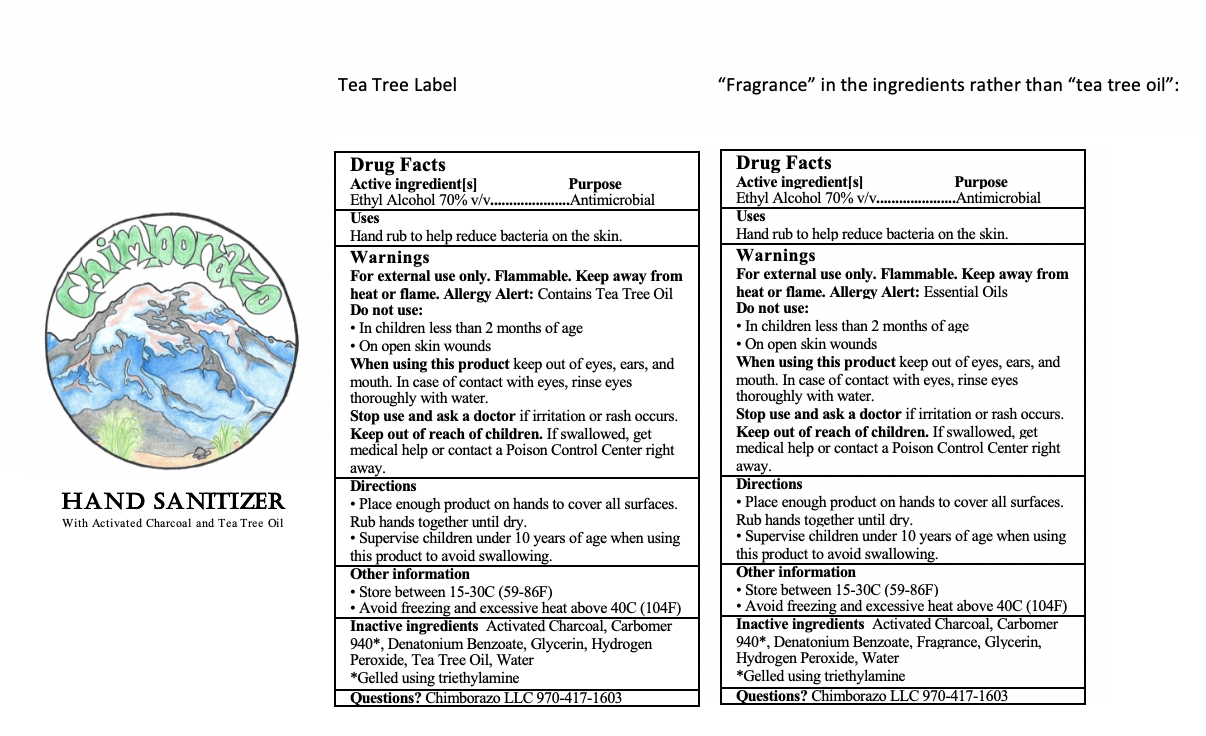 DRUG LABEL: Chimborazo Hand Sanitizer
NDC: 80052-001 | Form: GEL
Manufacturer: Chimborazo LLC
Category: otc | Type: HUMAN OTC DRUG LABEL
Date: 20201216

ACTIVE INGREDIENTS: ALCOHOL 0.7 mL/1 mL
INACTIVE INGREDIENTS: DENATONIUM BENZOATE 0.000005 mL/1 mL; GLYCERIN 0.01 mL/1 mL; HYDROGEN PEROXIDE 0.004 mL/1 mL; LAVENDER OIL 0.0017 mL/1 mL; TEA TREE OIL 0.0017 mL/1 mL; WATER 0.2742 mL/1 mL; CARBOMER 940 0.005 mL/1 mL; TRIETHYLAMINE 0.002 mL/1 mL; ACTIVATED CHARCOAL 0.0001 mL/1 mL

This is a hand sanitizer manufactured according to the FDA OTC Hand Sanitizer Monograph. The hand sanitizer is manufactured using only the following ingredients in the preparation of the product (percentage in final product formulation) consistent with World Health Organization (WHO) and Center for Disease Control (CDC) recommendations:

1. Alcohol (ethanol) (USP or Food Chemical Codex (FCC) grade) (70%, volume/volume (v/v)) in an aqueous solution denatured according to Alcohol and Tobacco Tax and Trade Bureau regulations in 27 CFR part 20.
2. Glycerin (1.00% v/v).
3. Hydrogen peroxide (0.125% v/v).
4. Sterile water or boiled cold water.
5. Carbomer 940 (<0.5% v/v)
6. Tea Tree Oil (0.17% v/v)
7. Lavender Oil (0.17% v/v)
8. Triethylamine (<0.2% v/v)
9. Trace amounts of activated charcoal from filtration of the ethanol

Active Ingredient(s)

Alcohol 70% v/v. Purpose: Antiseptic

Purpose

Antiseptic, Hand Sanitizer

Use

Hand Sanitizer to help reduce bacteria on the skin.

Warnings

For external use only. Flammable. Keep away from heat or flame. Allergy Alert: Contains Tea Tree Oil.

Do not use

- in children less than 2 months of age
- on open skin wounds

When using this product keep out of eyes, ears, and mouth. In case of contact with eyes, rinse eyes thoroughly with water.
Stop use and ask a doctor if irritation or rash occurs. Keep out of reach of children. If swallowed, get medical help or contact a Poison

Control Center right away.

Stop use and ask a doctor if irritation or rash occurs. These may be signs of a serious condition.

Keep out of reach of children. If swallowed, get medical help or contact a Poison Control Center right away.

Directions

- Place enough product on hands to cover all surfaces. Rub hands together until dry.
- Supervise children under 10 years of age when using this product to avoid swallowing.

Other information

- Store between 15-30C (59-86F)
- Avoid freezing and excessive heat above 40C (104F)

Inactive ingredients

glycerin, hydrogen peroxide, water, activated charcoal, carbomer 940, denatonium benzoate, tea tree oil

Uses

Hand rub to help reduce bacteria on the skin.

Directions

- Place enough product on hands to cover all surfaces. Rub hands until dry.

- Supervise children under 10 years of age when using this product to avoid swallowing.

Package Label - Principal Display Panel

General Label:

60 mL OR 2 oz. NDC: 80052-001-01:

240 mL OR 8 oz. NDC: 80052-001-02

3785 mL OR 128 oz. NDC: 80052-001-03